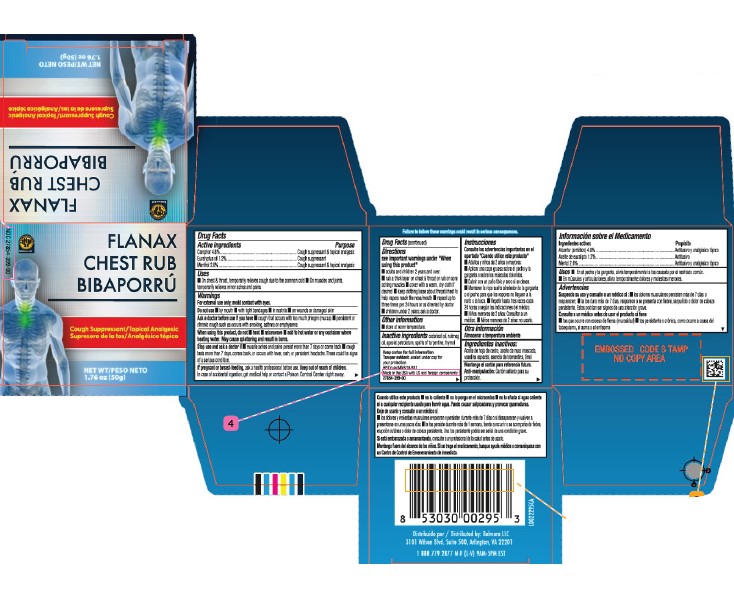 DRUG LABEL: Chest Rub
NDC: 27854-399 | Form: JELLY
Manufacturer: Belmora LLC
Category: otc | Type: HUMAN OTC DRUG LABEL
Date: 20260129

ACTIVE INGREDIENTS: MENTHOL 26 mg/1 g; CAMPHOR (SYNTHETIC) 48 mg/1 g; EUCALYPTUS OIL 12 mg/1 g
INACTIVE INGREDIENTS: CEDAR LEAF OIL; NUTMEG OIL; PETROLATUM; THYMOL; TURPENTINE OIL

Flanex 248.001/248AI
Medicated Chest Rub

Warning

Failure to follow these warnings could result in serious consequences.

Active ingredients

Camphor 4.8%

Eucalyptus oil 1.2%

Menthol 2.6%

Uses

- on chest & throat, temporarily relieves cough due to the common cold
- on muscles and joints, temporarily relieves minor aches and pains

Warnings

For external use only: avoid contact with eyes.

Do not use

- by mouth
- with tight bandages
- in nostrils
- on wounds or damaged skin

Ask a doctor before use if you have

- cough that occurs with too much phlegm (mucus)
- persistent or chronic cough such as occurs with smoking, asthma or emphysema

When using this product, do not

- heat
- microwave
- add to hot water or any container where heating water. May cause splattering and result in burns.

Stop use and ask a doctor if

- muscle aches and pains persist more than 7 days or come back
- cough lasts more than 7 days, comes back, or occurs with fever, rash, or persistent headache. These could be signs of a serious condition.

If pregnant or breast-feeding,

ask a health professional before use.

Keep out of reach of children.

In case of accidental ingestion, get medical help or contact a Poison Control Center right away.

Directions

see important warnings under “When using this product”

- adults & children 2 yrs & over:
- rub a thick layer on chest & throat or rub on sore aching muscles
- cover with a warm, dry cloth if desired
- keep clothing loose about throat/chest to help vapors reach the nose/mouth
- repeat up to three times per 24 hours or as directed by doctor
- children under 2 years of age: ask a doctor

Other information

- store at room temperature

Inactive ingredients

cedarleaf oil, nutmeg oil, special petrolatum, spirits of turpentine, thymol

Disclaimer

Keep carton for full information

Tamper Evident Statement

Tamper evident: sealed under cap for your protection.

Adverse Reaction

Made in the USA with US and foreign components.

27854-399-00

Distributed by: Belmora LLC

3101 Wilson Blvd. Suite 500, Arlington, VA 22201

1 888 779 2877 M-F (L-V) 9AM-5PM EST

Purpose

Cough suppressant & topical analgesic

Principal Display Panel

NDC 27854-399-00

FLANAX

CHEST RUB

Cough Suppressant / Topical Analgesic

NET WT 1.76 oz (50 g)